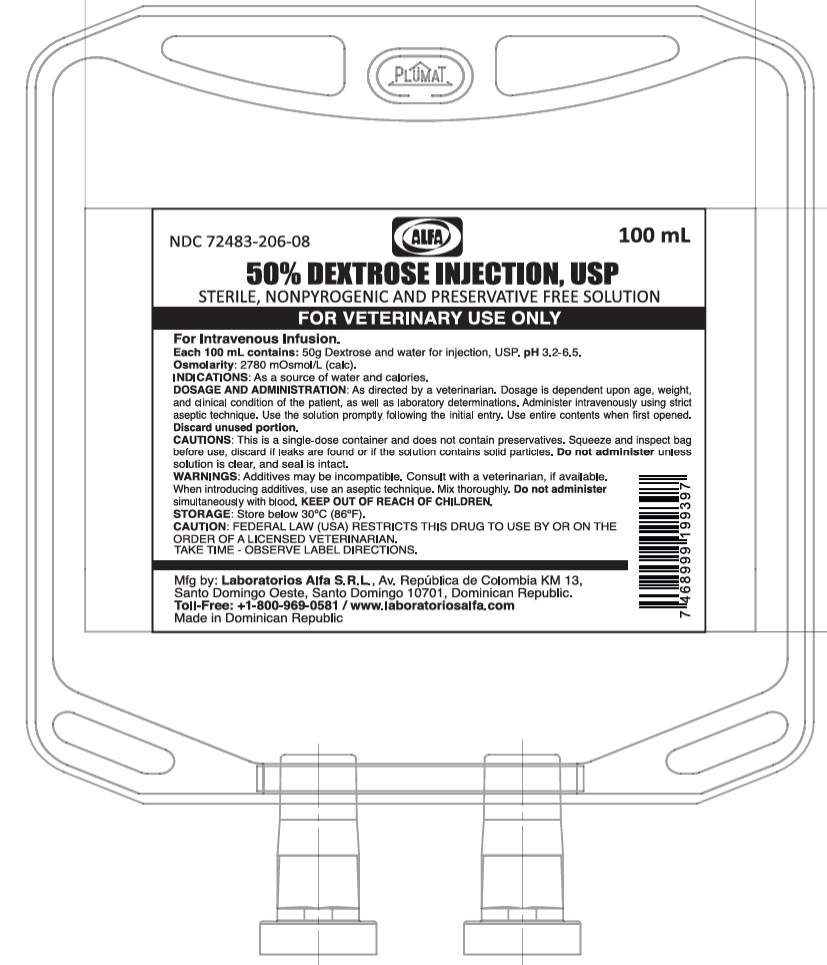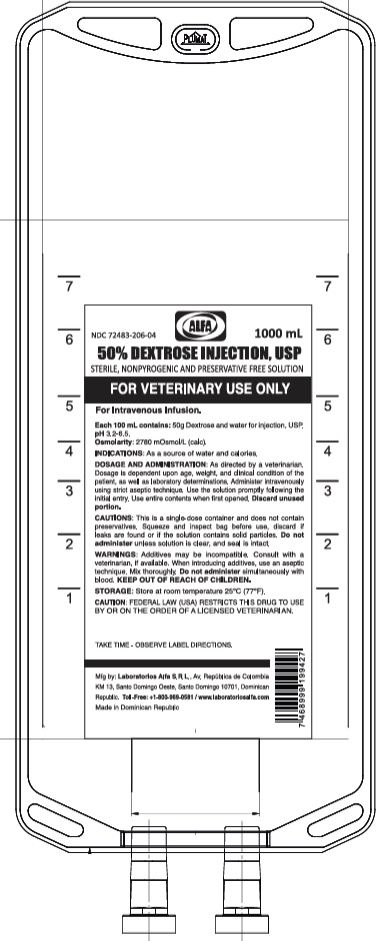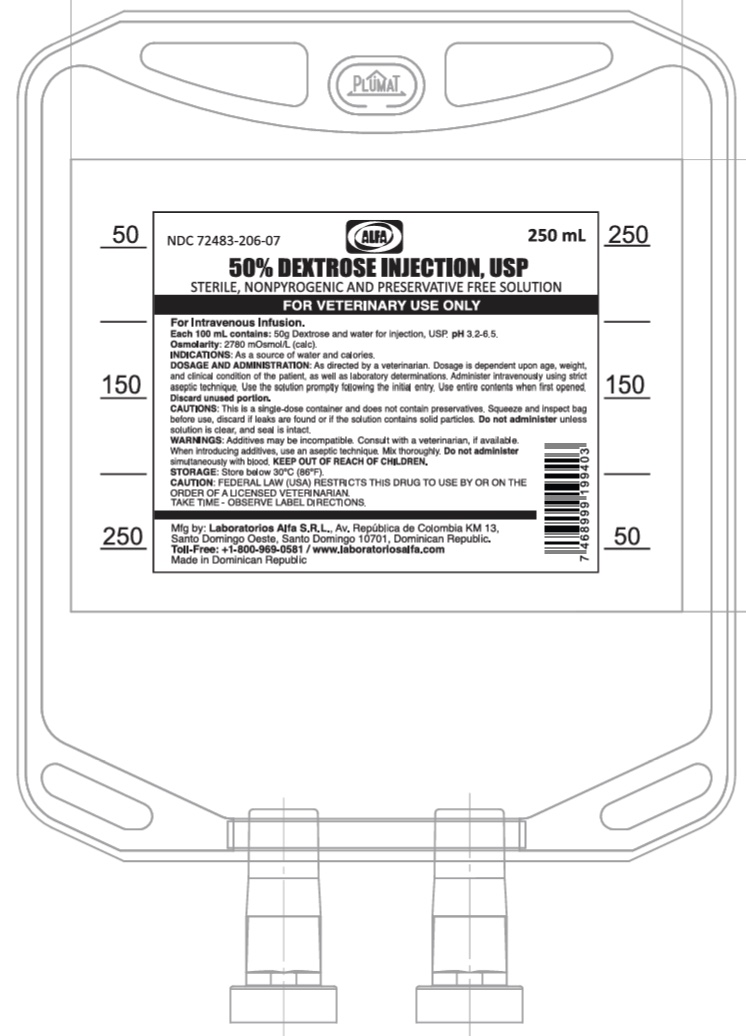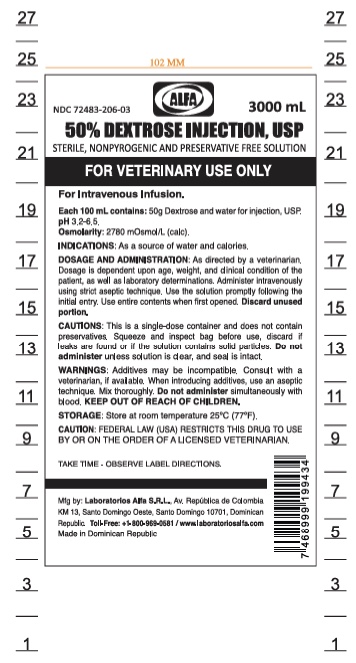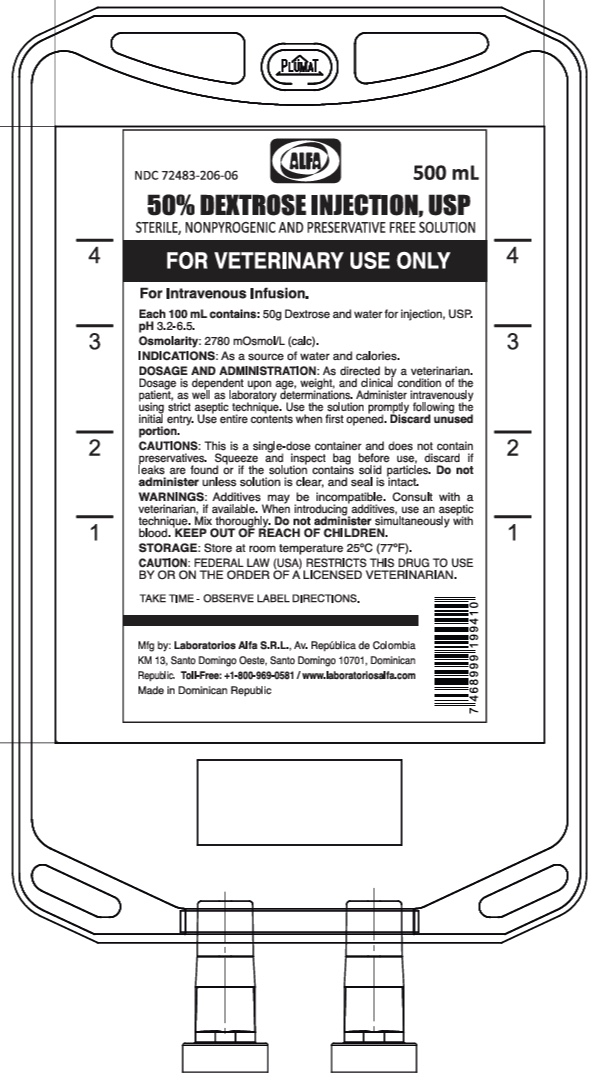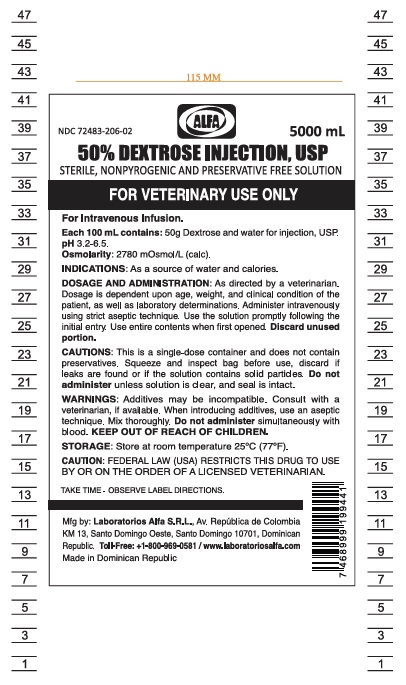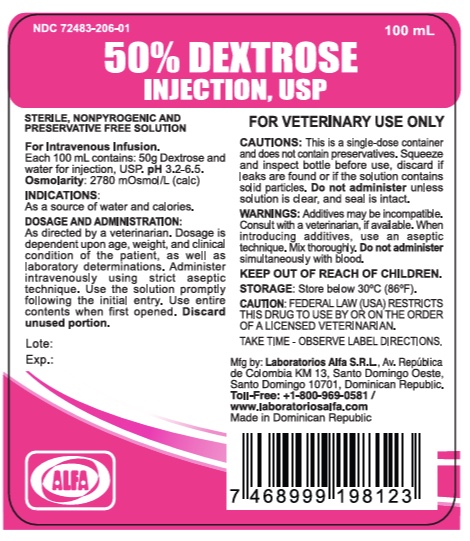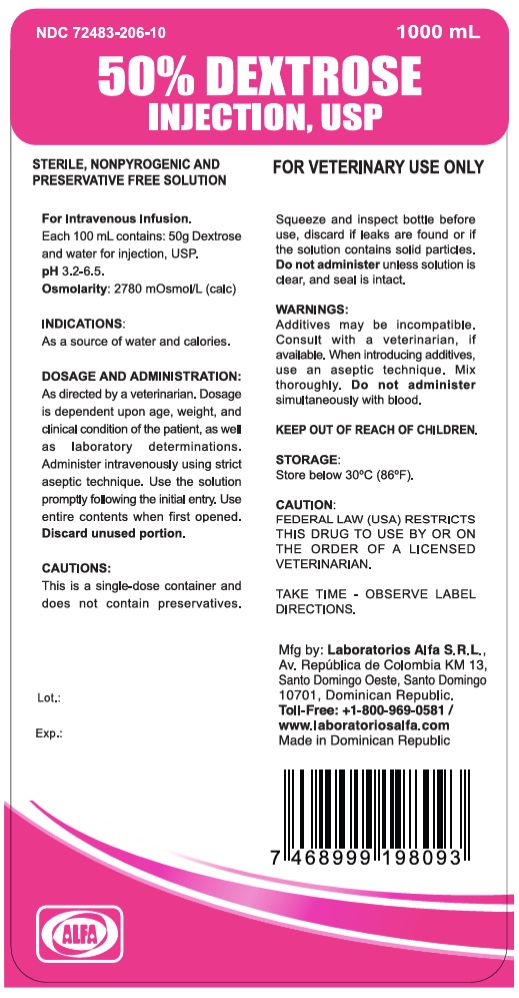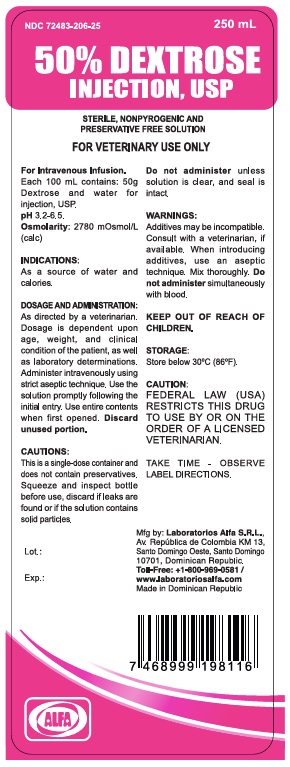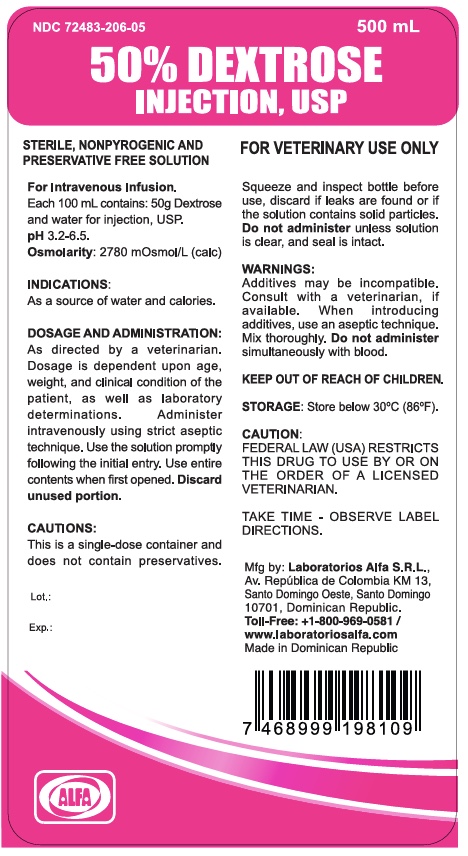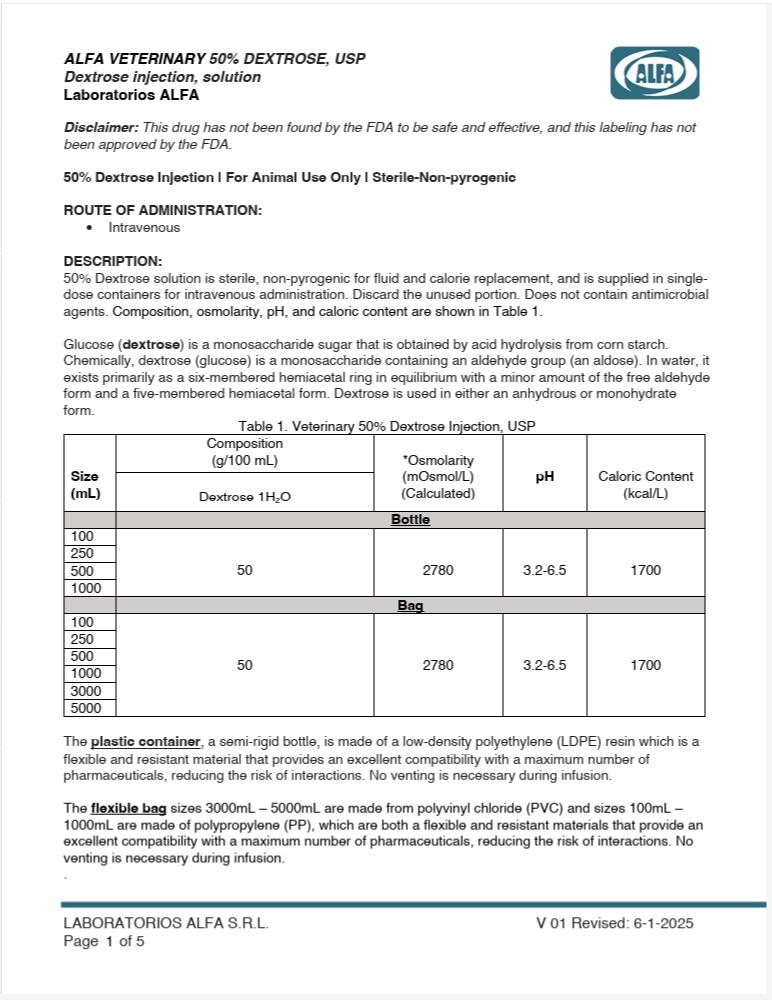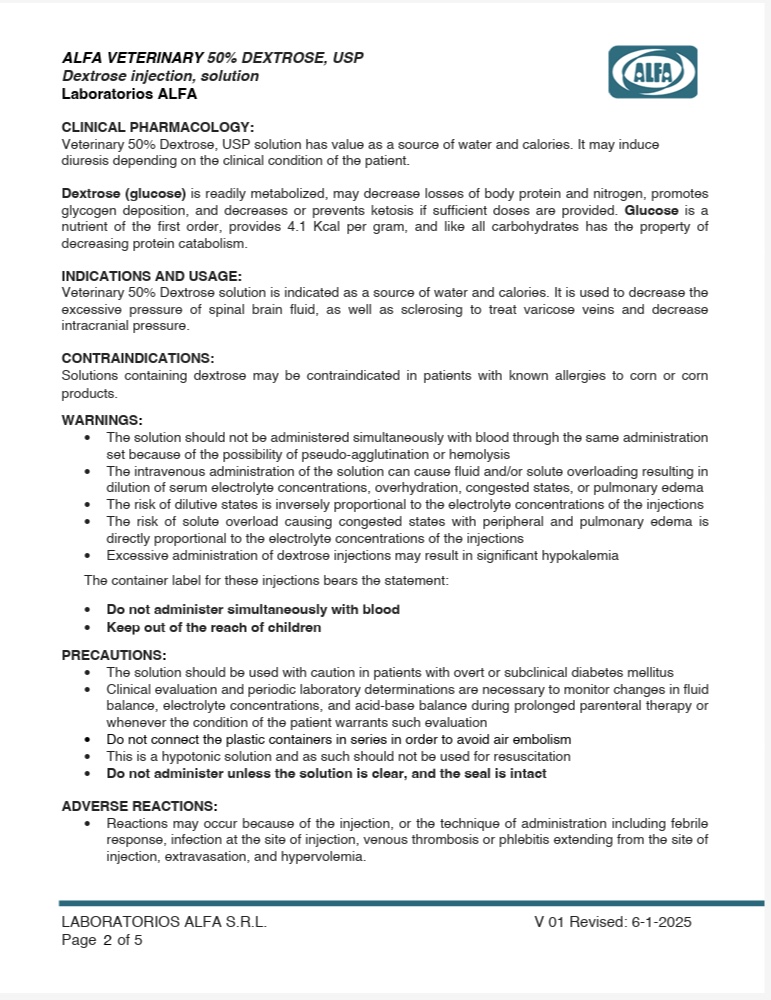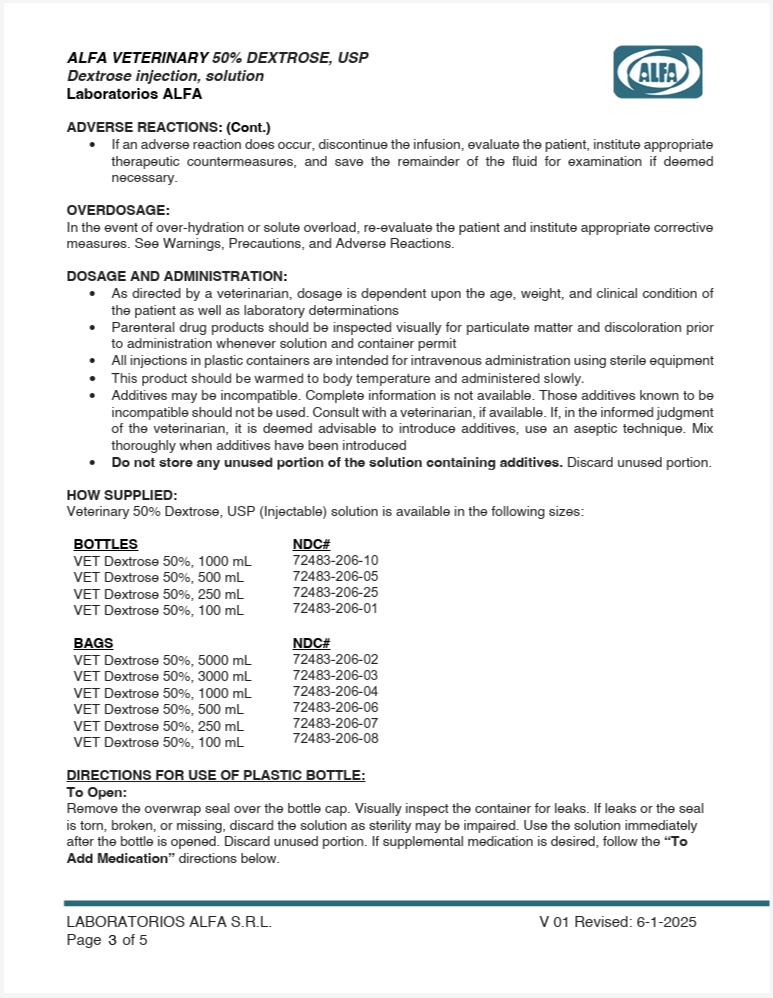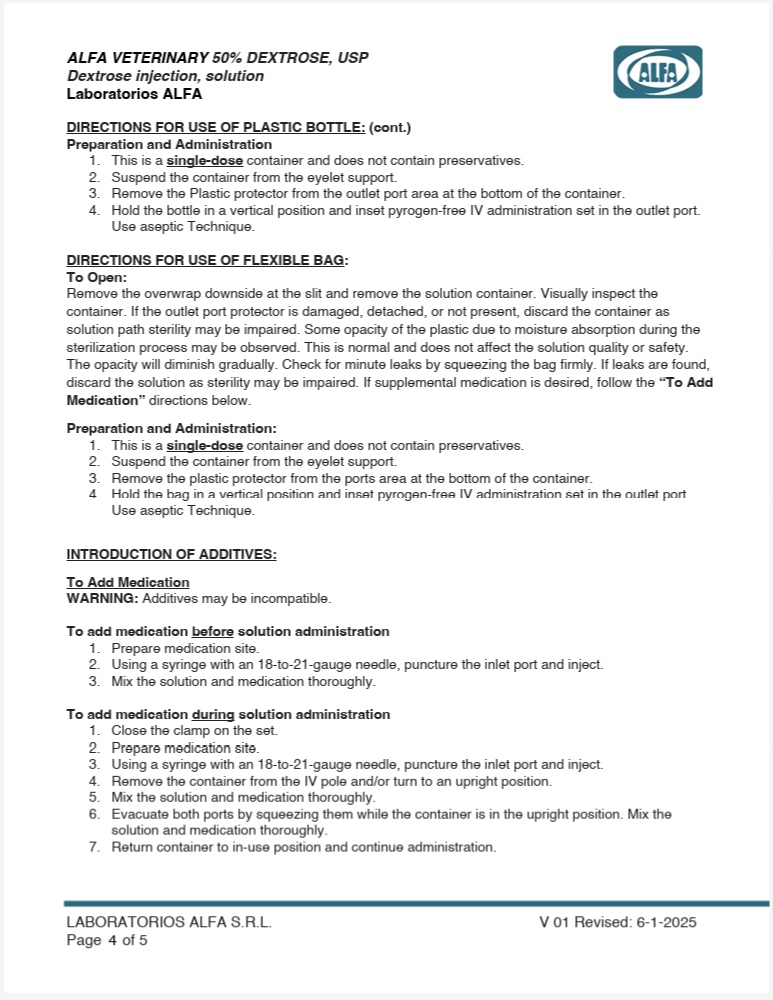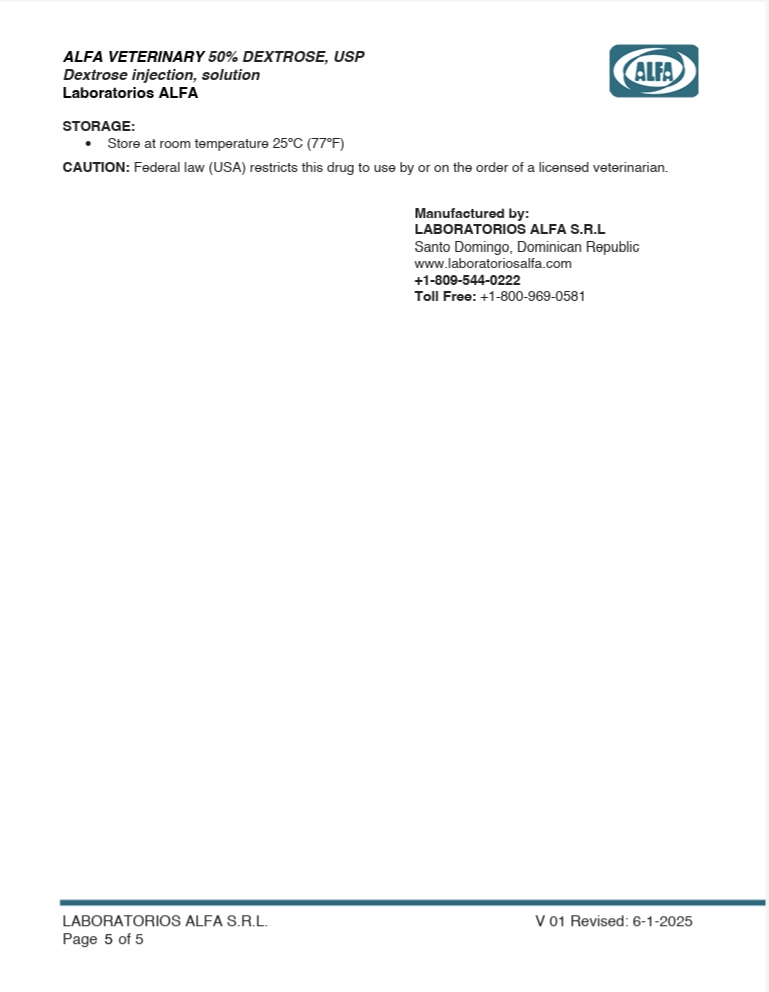 DRUG LABEL: Alfa Veterinary 50% Dextrose
NDC: 72483-206 | Form: INJECTION, SOLUTION
Manufacturer: Laboratorios Alfa SRL
Category: animal | Type: PRESCRIPTION ANIMAL DRUG LABEL
Date: 20250814

ACTIVE INGREDIENTS: DEXTROSE MONOHYDRATE 5000 mg/100 mL
INACTIVE INGREDIENTS: WATER

DESCRIPTION

50% dextrose solution is sterile, non-pyrogenic for fluid and calorie replacement, and is supplied in single-dose containers for intravenous administration. Discard the unused portion. Does not contain antimicrobial agents.

Glucose (dextrose) is a monosaccharide sugar that is obtained by acid hydrolysis of corn starch. Chemically, glucose contains a pyramidal ring-5-atom of carbon and one of oxygen and in aqueous solution, there are two forms that are in equilibrium with the aldehyde form. The use can be anhydrous or with a water molecule.

The Plastic container, a semi-rigid bottle, is made of a low density polyethylene which is a flexible and resistant material that provides an excellent compatibility with a maximum number of pharmaceuticals, reducing the risk of interactions. No venting is necessary during infusion.

Table 1. Veterinary 50% Dextrose Injection, USP
Size (mL) | Composition (g/100 mL) | *Osmolarity (mOsmol/L) (Calculated) | pH | Caloric Content (kcal/L)
Size (mL) | Dextrose 1H2 | *Osmolarity (mOsmol/L) (Calculated) | pH | Caloric Content (kcal/L)
100 | 50 | 2780 | 3.2-6.5 | 1700
250 | 50 | 2780 | 3.2-6.5 | 1700
500 | 50 | 2780 | 3.2-6.5 | 1700
1000 | 50 | 2780 | 3.2-6.5 | 1700

No venting is necessary during infusion.

CLINICAL PHARMACOLOGY

Veterinary 50% Dextrose Injection, USP solution has value as a source of water and calories. It is capable of inducing diuresis depending on the clinical condition of the patient.

Glucose is a nutrient of the first order, provides 4.1 Kcal per gram and like all carbohydrates has the property of decreasing protein catabolism

INDICATIONS AND USAGE

50% dextrose solution is indicated as a source of water and calories. It is used to decrease the excessive pressure of spinal brain fluid, also as sclerosing to treat varicose veins and decrease intracranial pressure

WARNING

Veterinary 50% Dextrose Injection, USP should not be administered simultaneously with blood through the same administration set because of the possibility of pseudo agglutination or hemolysis.

The intravenous administration of 5% Dextrose Injection can cause fluid and/or solute overloading resulting in dilution of serum electrolyte concentrations, over hydration, congested states, or pulmonary edema.

The risk of dilutive states is inversely proportional to the electrolyte concentrations of the injections.

The risk of solute overload causing congested states with peripheral and pulmonary edema is directly proportional to the electrolyte concentrations of the injections.

Excessive administration of dextrose injections may result in significant hypokalemia.

The container label for these injections bears the statement: Do not administer simultaneously with blood.
Keep out of the reach of children.

ADVERSE REACTIONS

Reactions which may occur because of the injection or the technique of administration include febrile response, infection at the site of injection, venous thrombosis or phlebitis extending from the site of injection, extravasation and hypervolemia.

If an adverse reaction does occur, discontinue the infusion, evaluate the patient, institute appropriate therapeutic countermeasures and save the remainder of the fluid for examination if deemed necessary.

PRECAUTIONS

Veterinary 50% Dextrose Injection, USP should be used with caution in patients with known overt or subclinical diabetes mellitus.

Clinical evaluation and periodic laboratory determinations are necessary to monitor changes in fluid balance, electrolyte concentrations and acid base balance during prolonged parenteral therapy or whenever the condition of the patient warrants such evaluation.

This is a hypotonic solution and as such should not be used for resuscitation.

Do not administer unless solution is clear and both seal and container are intact.

DOSAGE AND ADMINISTRATION

As directed by a veterinarian. Dosage is dependent upon the age, weight and clinical condition of the patient as well as laboratory determinations.

Parenteral drug products should be inspected visually for particulate matter and discoloration prior to administration whenever solution and container permit.

All injections in plastic containers are intended for intravenous administration using sterile equipment.

Additives may be incompatible. Complete information is not available. Those additives known to be incompatible should not be used. Consult with veterinarian, if available. If, in the informed judgment of the veterinarian, it is deemed advisable to introduce additives, use aseptic technique. Mix thoroughly when additives have been introduced.

Do not store solutions containing additives. Discard unused portion.

OVERDOSAGE

In an event of over hydration or solute overload, re-evaluate the patient and institute appropriate corrective measures. See Warnings, Precautions, and Adverse Reactions.

STORAGE

Store below 30ºC (86ºF).

PRECAUTION FOR USE OF THE BOTTLE

This is a single dose container and does not contain preservatives.

Use the solution immediately after the bottle is opened, discard the remaining one.
Squeeze and inspect the bottle, discard if leaks are found or if the solution contains visible and solid particles.

Do not administer simultaneously with blood.
Do not use it unless solution is clear, and seal is intact.

DIRECTIONS FOR USE PLASTIC CONTAINER:

This is a single dose container and does not contain preservatives. If leaks are found, discard solution as sterility may be impaired. Use the solution immediately after the bottle is opened, discard the remaining one. Discard unused portion. If supplemental medication is desired follow directions below:

Preparation and administration
1. Check for minute leaks by squeezing the container firmly. If leaks are found, discard solution as sterility may be impaired.
2. Suspend container from eyelet support.
3. Remove Plastic protector from ports area at the bottom of container.
4. Hold the bottle in vertical position and inset pyrogen free IV administration set in the outlet port. Use aseptic Technique

To add medication
WARNING: Additives may be incompatible.
To add medication before solution administration
1. Prepare medication site.
2. Using syringe with 18 to 21 gauge needle, puncture inlet port and inject.
3. Mix solution and medication thoroughly.

To add medication during solution administration
1. Close clamp on the set.
2. Prepare medication site.
3. Using syringe with 18 to 21 gauge needle, puncture inlet port and inject.
4. Remove container from IV pole and/or turn to an upright position.
5. Mix solution and medication thoroughly.
6. Return container to in use position and continue administration.

CAUTION: Federal law (USA) restricts this drug to use by or on the order of a licensed veterinarian.

PACKAGE INSERT

For Animal Use Only

Dextrosa 50% (Bottles)

Veterinary 5% Dextrose Injection,USP

NDC: :72483-206-10 1000 mL 50% Dextrose

NDC: 72483-206-05 500 mL 50% Dextrose

NDC: 72483-206-25 250 mL 50% Dextrose

NDC: 72483-206-01 100 mL 50% Dextrose

Dextrosa 50% (Bags)

Veterinary 5% Dextrose Injection, USP

NDC: :72483-206-02 5000 mL 50% Dextrose

NDC: :72483-206-03 3000 mL 50% Dextrose

NDC: :72483-206-04 1000 mL 50% Dextrose

NDC: 72483-206-06 500 mL 50% Dextrose

NDC: 72483-206-07 250 mL 50% Dextrose

NDC: 72483-206-08 100 mL 50% Dextrose